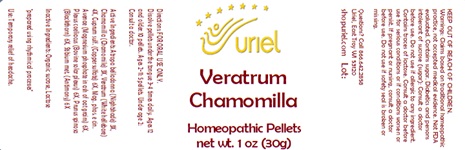 DRUG LABEL: Veratrum Chamomilla
NDC: 48951-9038 | Form: PELLET
Manufacturer: Uriel Pharmacy Inc.
Category: homeopathic | Type: HUMAN OTC DRUG LABEL
Date: 20240307

ACTIVE INGREDIENTS: ATROPA BELLADONNA 3 [hp_X]/1 1; MATRICARIA RECUTITA 3 [hp_X]/1 1; VERATRUM ALBUM ROOT 4 [hp_X]/1 1; CUPRIC SULFATE 6 [hp_X]/1 1; MAGNESIUM PHOSPHATE, TRIBASIC, PENTAHYDRATE 6 [hp_X]/1 1; BOS TAURUS NERVE 6 [hp_X]/1 1; SLOE 6 [hp_X]/1 1; ANTIMONY 6 [hp_X]/1 1
INACTIVE INGREDIENTS: SUCROSE

Veratrum Chamomilla

INDICATIONS AND USAGE

Directions: FOR ORAL USE ONLY.

DOSAGE AND ADMINISTRATION

Dissolve pellets under the tongue 3-4 times daily. Ages 12 and older: 10 pellets. Ages 2-11: 5 pellets. Under age 2: Consult a doctor.

ACTIVE INGREDIENT

Active Ingredients: Atropa belladonna (Nightshade) 3X, Chamomilla (Chamomile) 3X, Veratrum (White hellebore) 4X, Cuprum sulf. (Copper sulfate) 6X, Mag. phos. e cin. Avenae (Magnesium phosphate in ash of oat grains) 6X, Plexus coeliacus (Bovine solar plexus) 6X, Prunus spinosa (Blackthorn) 6X, Stibium met. (Antimony) 6X

Inactive Ingredient: Organic sucrose

"prepared using rhythmical processes"

PURPOSE

Use: Temporary relief of headache.

KEEP OUT OF REACH OF CHILDREN.

WARNINGS

Warnings: Claims based on traditional homeopathic practice, not accepted medical evidence. Not FDA evaluated. Contains sugar. Diabetics and persons intolerant of sucrose (sugar): Consult a doctor before use. Contains traces of lactose. Do not use if allergic to any ingredient. Consult a doctor before use for serious conditions or if conditions worsen or persist. If pregnant or nursing, consult a doctor before use. Do not use if safety seal is broken or missing.

QUESTIONS

Questions? Call 866.642.2858 Uriel, East Troy, WI 53120 shopuriel.com Lot: